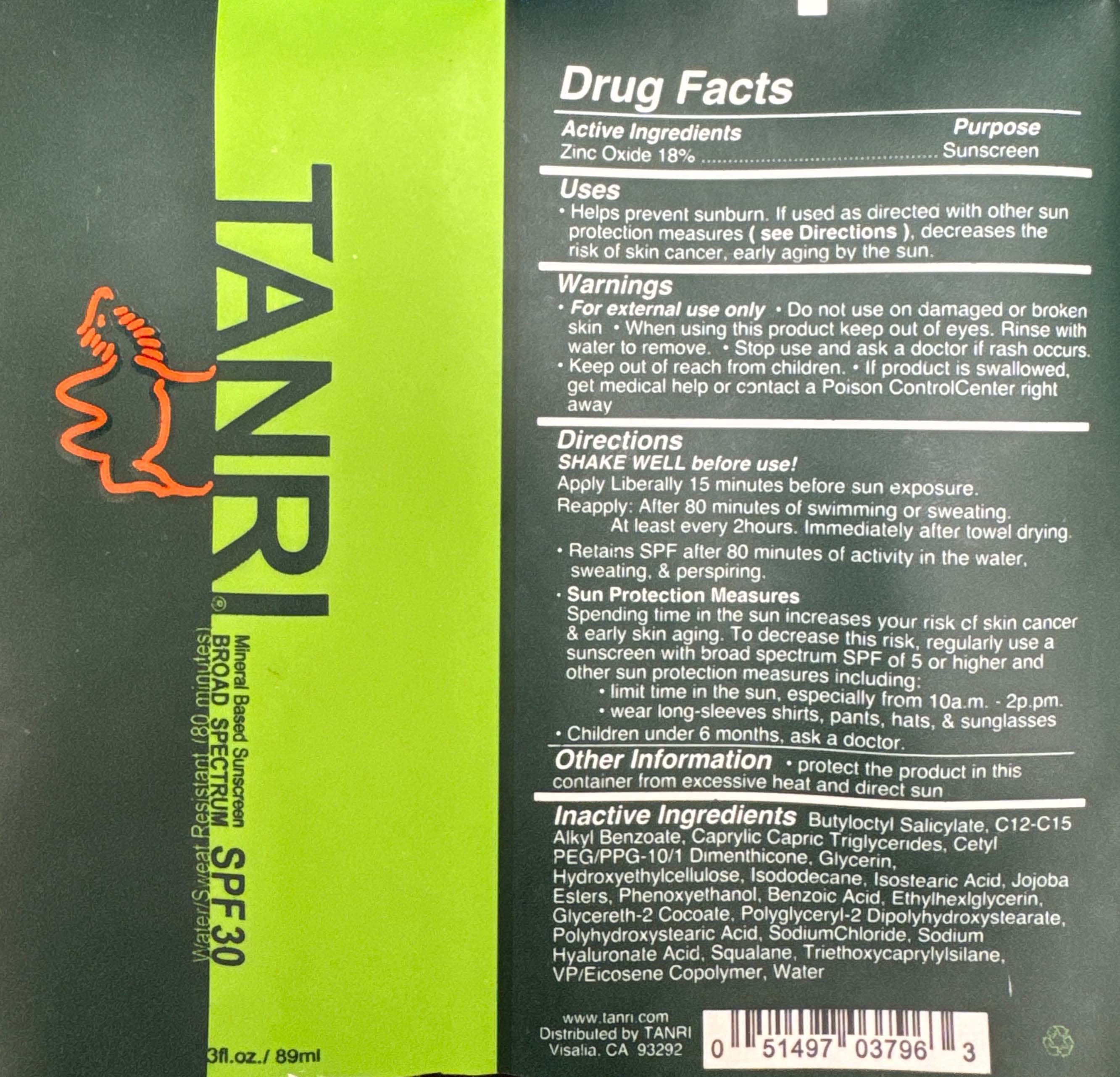 DRUG LABEL: Tanri Broad Spectrum SPF 30
NDC: 65112-305 | Form: LOTION
Manufacturer: I. Shay Cosmetics
Category: otc | Type: HUMAN OTC DRUG LABEL
Date: 20260210

ACTIVE INGREDIENTS: ZINC OXIDE 0.18 g/89 mL
INACTIVE INGREDIENTS: WATER

Tanri SPF 30

ACTIVE INGREDIENT

Zinc Oxide – 36%

PURPOSE

Sunscreen

WARNING: Keep out of reach of children

INDICATIONS AND USAGE

Helps prevent sunburn. If used as directed with other sun protection measures, decreases the risk of skin cancer, early aging by the sun.

INACTIVE INGREDIENT

Purified Water

C12-C15 Alkyl Benzoate

Isostearic Acid

Polyhydroxystearic Acid

Butyloctyl Salicylate

Caprylic Capric Triglycerides

Cetyl/ PEG/ PPG-10/ 1 Dimethicone

Glycerin

Hydroxyethyl Cellulose

Isododecane

Jojoba Esters

Phenoxyethanol

Benzoic Acid

Ethylhexylglycerin

Glycereth-2 Cocoate

Polyglyceryl-2 Dipolyhydroxystearate

Sodium Chloride

Sodium Hyaluronate Acid

Squalane

Triethoxycaprylylsilane

Eicosene Copolymer

WARNINGS

For external use only.

Do not use on damaged or broken skin.

When using this product keep out of eyes.

Rinse with water to remove.

Stop use and ask a doctor if rash occurs.

Keep out of reach of children.

If product is swallowed, get medical help or contact a Poison Control Center right away.

DOSAGE AND ADMINISTRATION

Shake well before use.

Apply liberally 15 minutes before sun exposure.

Reapply: after 80 minutes of swimming or sweating; at least every 2 hours; Immediately after towel drying.

Retains SPF after 80 minutes of activity in the water, sweating & perspiring.

Sun Protection Measures: Spending time in the sun increases your risk of skin cancer & early skin aging. To decrease this risk, Regularly use a sunscreen with broad spectrum SPF of 5 or higher and other sun protection measures including:

- limit time in the sun, especially from 10a.m. - 2p.m.

- wear long-sleeves shirts, pants, hats, & sunglasses

Children under 6 months, ask a doctor.